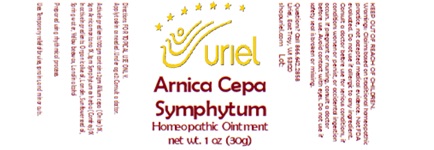 DRUG LABEL: Arnica Cepa Symphytum
NDC: 48951-1390 | Form: OINTMENT
Manufacturer: Uriel Pharmacy, Inc
Category: homeopathic | Type: HUMAN OTC DRUG LABEL
Date: 20250103

ACTIVE INGREDIENTS: COMFREY ROOT 1 [hp_X]/1 g; ONION 1 [hp_X]/1 g; ARNICA MONTANA 1 [hp_X]/1 g
INACTIVE INGREDIENTS: BEESWAX; LANOLIN ALCOHOL; OLIVE OIL; SUNFLOWER OIL; LANOLIN; WATER

Arnica Cepa Symphytum

INDICATIONS AND USAGE

Directions: FOR TOPICAL USE ONLY.

DOSAGE AND ADMINISTRATION

Apply to skin as needed. Under age 2: Consult a doctor.

ACTIVE INGREDIENT

Active Ingredients: 100gm contains: 2gm Allium cepa (Onion) 1X, 5gm Arnica montana 1X, 3gm Symphytum ex herba (Comfrey) 1X

INACTIVE INGREDIENT

Inactive Ingredients: Organic olive oil, Lanolin, Sunflower seed oil, Spring water, Yellow beeswax, Lanolin alcohol

Prepared using rhythmical processes.

PURPOSE

Uses: Temporary relief of bruises, sprains, and minor cuts.

KEEP OUT OF REACH OF CHILDREN.

WARNINGS

Warnings: Claims based on traditional homeopathic practice, not accepted medical evidence. Not FDA evaluated. Do not use if allergic to any ingredient. Consult a doctor before use for serious conditions, if conditions worsen or persist, or accidental ingestion occurs. If pregnant or nursing, consult a doctor before use. Avoid contact with eyes. Do not use if safety seal is broken or missing.

Questions? Call 866.642.2858
Uriel, East Troy, WI 53120
shopuriel.com Lot: